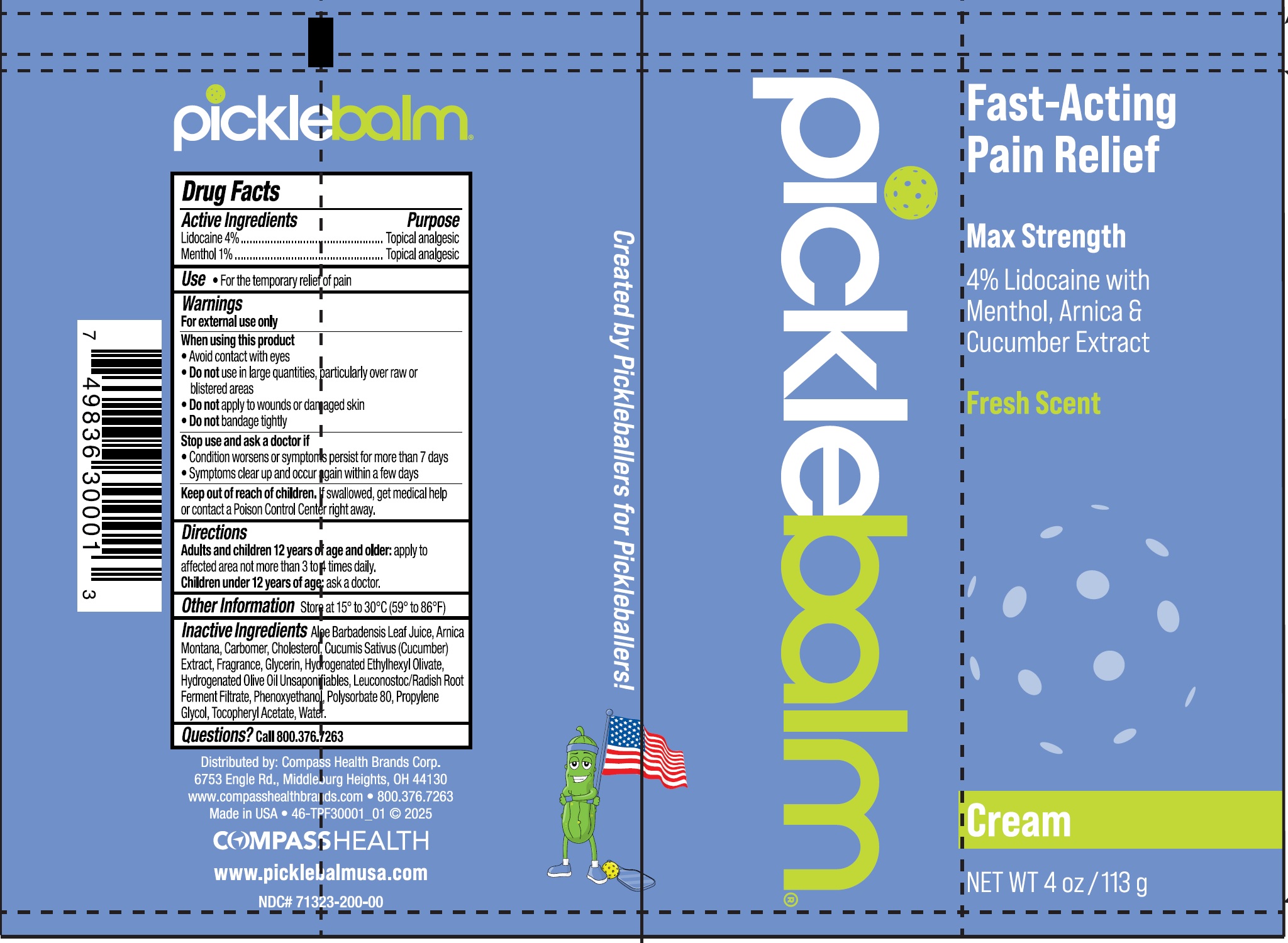 DRUG LABEL: PICKLEBALM LIDOCAINE WITH MENTHOL ARNICA CUCUMBER SEED
NDC: 71323-200 | Form: CREAM
Manufacturer: Compass Health Brands Corp.
Category: otc | Type: HUMAN OTC DRUG LABEL
Date: 20250422

ACTIVE INGREDIENTS: LIDOCAINE 40 mg/1 g; MENTHOL 10 mg/1 g
INACTIVE INGREDIENTS: ALOE VERA LEAF JUICE; ARNICA MONTANA WHOLE; CARBOMER HOMOPOLYMER, UNSPECIFIED TYPE; CHOLESTEROL; CUCUMBER; GLYCERIN; HYDROGENATED ETHYLHEXYL OLIVATE; HYDROGENATED OLIVE OIL UNSAPONIFIABLES; LEUCONOSTOC/RADISH ROOT FERMENT FILTRATE; PHENOXYETHANOL; POLYSORBATE 80; PROPYLENE GLYCOL; .ALPHA.-TOCOPHEROL ACETATE; WATER

PICKLEBALM LIDOCAINE WITH MENTHOL ARNICA CUCUMBER SEED CREAM

Active Ingredients

Lidocaine 4%

Menthol 1%

Purpose

Topical analgesic

Use

- For the temporary relief of pain

Warnings

For external use only

When using this product

- Avoid contact with eyes
- Do notuse in large quantities, particularly over raw or blistered areas
- Do notapply to wounds or damaged skin
- Do notbandage tightly

Stop use and ask a doctor if:

- Condition worsens or symptoms persist for more than 7 days
- Symptoms clear up and occur again within a few days

Keep out of reach of children.

If swallowed, get medical help or contact a Poison Control Center right away.

Directions

Adults and children 12 years of age and older:apply to affected area not more than 3 to 4 times daily.

Children under 12 years of age: ask a doctor.

Other Information

- Store at 15° to 30°C (59° to 86°F)

Inactive ingredients:

Aloe Barbadensis Leaf Juice, Arnica Montana, Carbomer, Cholesterol, Cucumis Sativus (Cucumber) Extract, Fragrance, Glycerin, Hydrogenated Ethylhexyl Olivate, Hydrogenated Olive Oil Unsaponifiables, Leuconostoc/Radish Root Ferment Filtrate, Phenoxyethanol, Polysorbate 80, Propylene Glycol, Tocopheryl Acetate, Water.

Questions?

Call 800.376.7263